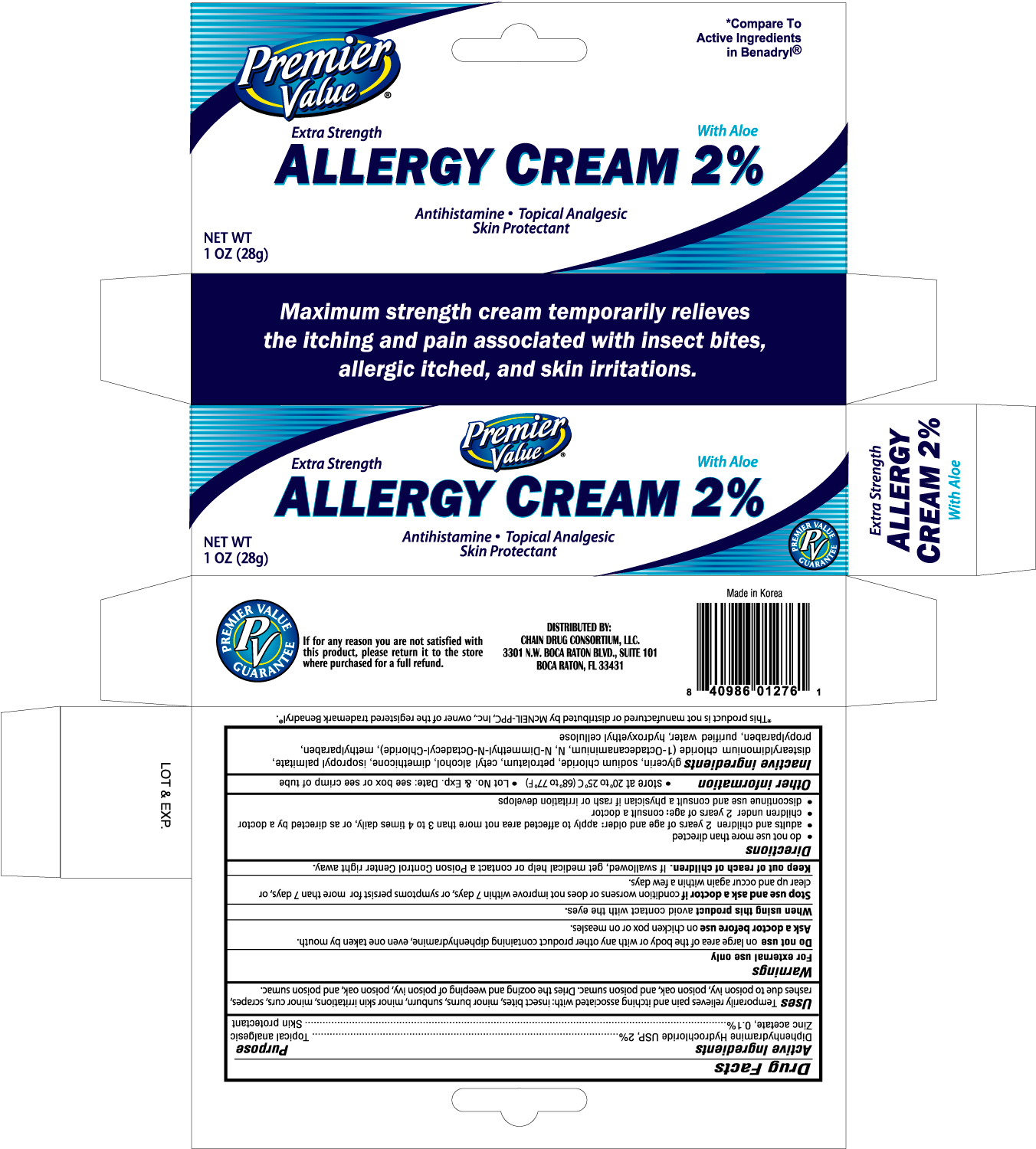 DRUG LABEL: PREMIER VALUE ALLERGY 
NDC: 68169-0127 | Form: CREAM
Manufacturer: TAI GUK PHARM. CO., LTD.
Category: otc | Type: HUMAN OTC DRUG LABEL
Date: 20100917

ACTIVE INGREDIENTS: DIPHENHYDRAMINE HYDROCHLORIDE 2 g/100 g; ZINC ACETATE 0.1 g/100 g
INACTIVE INGREDIENTS: GLYCERIN; SODIUM CHLORIDE; PETROLATUM; CETYL ALCOHOL; DIMETHICONE; ISOPROPYL PALMITATE; DISTEARYLDIMONIUM CHLORIDE; METHYLPARABEN; PROPYLPARABEN; WATER

Drug Facts

Active Ingredients Purpose

Diphenhydramine Hydrochloride USP, 2% .........................................Topical analgesic

Zinc acetate, 0.1% .........................................................................Skin Protectant

Uses

Temporarily relieves pain and itching associated with: insect bites, minor burns, sunburn, minor skin irritations, minor cuts, scrapes, rashes due to poison ivy, poison oak, and poison sumac. Dries the oozing and weeping of poison ivy, poison oak, and poison sumac.

Warnings

For external use only

Do not use on large area of the body or with any other product containing diphenhydramine, even one taken by mouth.

Ask a doctor before use

on chicken pox or on measles.

When using this product

avoid contact with the eyes.

Stop use and ask a doctor if condition worsens or does not improve within 7 days, or symptoms persist for more than 7 days, or clear up and occur again within a few days.

Keep out of reach of children. If swallowed, get medical help or contact a Poison Control Center right away.

Directions

- do not use more than directed
- adults and children 2 years of age and older: apply to affected area not more than 3 to 4 times daily, or as directed by a doctor
- children under 2 years of age: consult a doctor
- discontinue use and consult a physician if rash or irritation develops

Other information

- store at 20o to 25oC (68o to 77oF)
- Lot No. and Exp. Date: see box or see crimp of tube

DOSAGE AND ADMINISTRATION

Distributed By:

Chain Drug Consortium, LLC.

3301 N.W. Boca Raton Blvd., Suite 101

Boca Raton, FL 33431

Inactive ingredients

glycerin, sodium chloride, petrolatum, cetyl alcoho, dimethicone, isopropyl palmitate, distearyldimonium chloride, methylparaben, propylparaben, purified water, hydroxyethyl cellulose

PACKAGE LABEL

Enter section text here